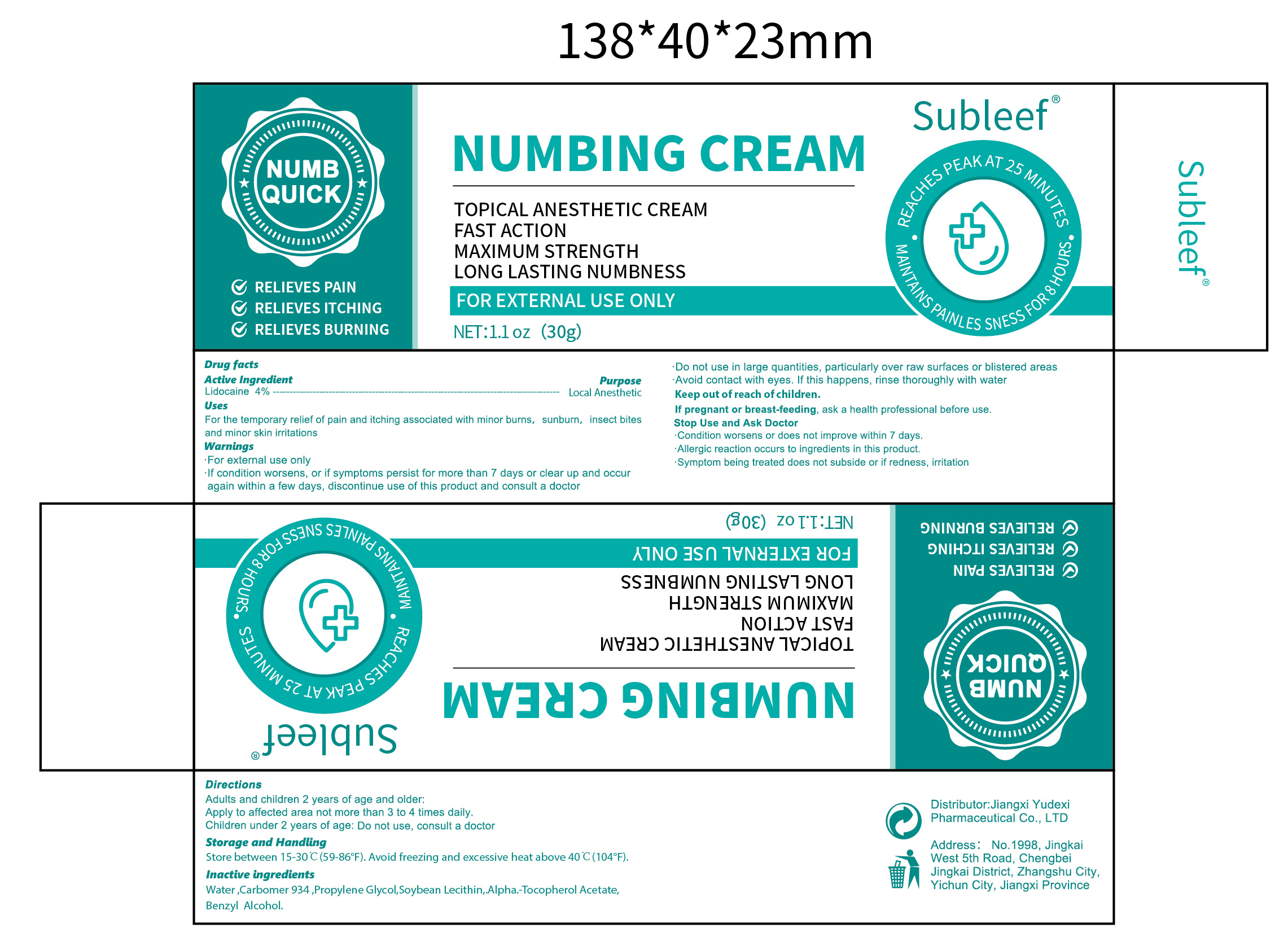 DRUG LABEL: Subleef   NUMBING
NDC: 85248-052 | Form: CREAM
Manufacturer: Jiangxi Yudexi Pharmaceutical Co., LTD
Category: otc | Type: HUMAN OTC DRUG LABEL
Date: 20260205

ACTIVE INGREDIENTS: LIDOCAINE 4 g/100 g
INACTIVE INGREDIENTS: WATER; PROPYLENE GLYCOL; SOYBEAN LECITHIN; BENZYL ALCOHOL; .ALPHA.-TOCOPHEROL ACETATE; CARBOMER 934

85248-052

Active Ingredient

Lidocaine 4%

Purpose

Local Anesthetic

Use

For the temporary relief of pain and itching associated with minor burns, sunburn, insect bites and minor skin irritations

Warnings

·For external use only. ·If condition worsens, or if symptoms persist for more than 7 days or clear up and occur again within a few days, discontinue use of this product and consult a doctor

·Do not use in large quantities, particularly over raw surfaces or blistered areas

When Using

·Avoid contact with eyes, lf this happens, rinse thoroughly with water.

Stop Use

·Condition worsens or does not improve within 7 days.·Allergic reaction occurs to ingredients in this product.·Symptom being treated does not subside or if redness, irritation

Ask Doctor

·Condition worsens or does not improve within 7 days.·Allergic reaction occurs to ingredients in this product.·Symptom being treated does not subside or if redness, irritation

Keep Oot Of Reach Of Children

If pregnant or breast-feeding, ask a health professional before use

Directions

Adults and children 2 years of age and older.Apply to affected area not more than 3 to 4 times daily.Children under 2 years of age: Do not use, consult a doctor

Other information

Store between 15-30℃(59-86F). Avoid freezing and excessive heat above 40 ℃(104°F).

Inactive ingredients

Water,Carbomer934, propylene Glycol,soybean Lecithin,.Alpha.-Tocopherol Acetate,Benzyl Alcohol.